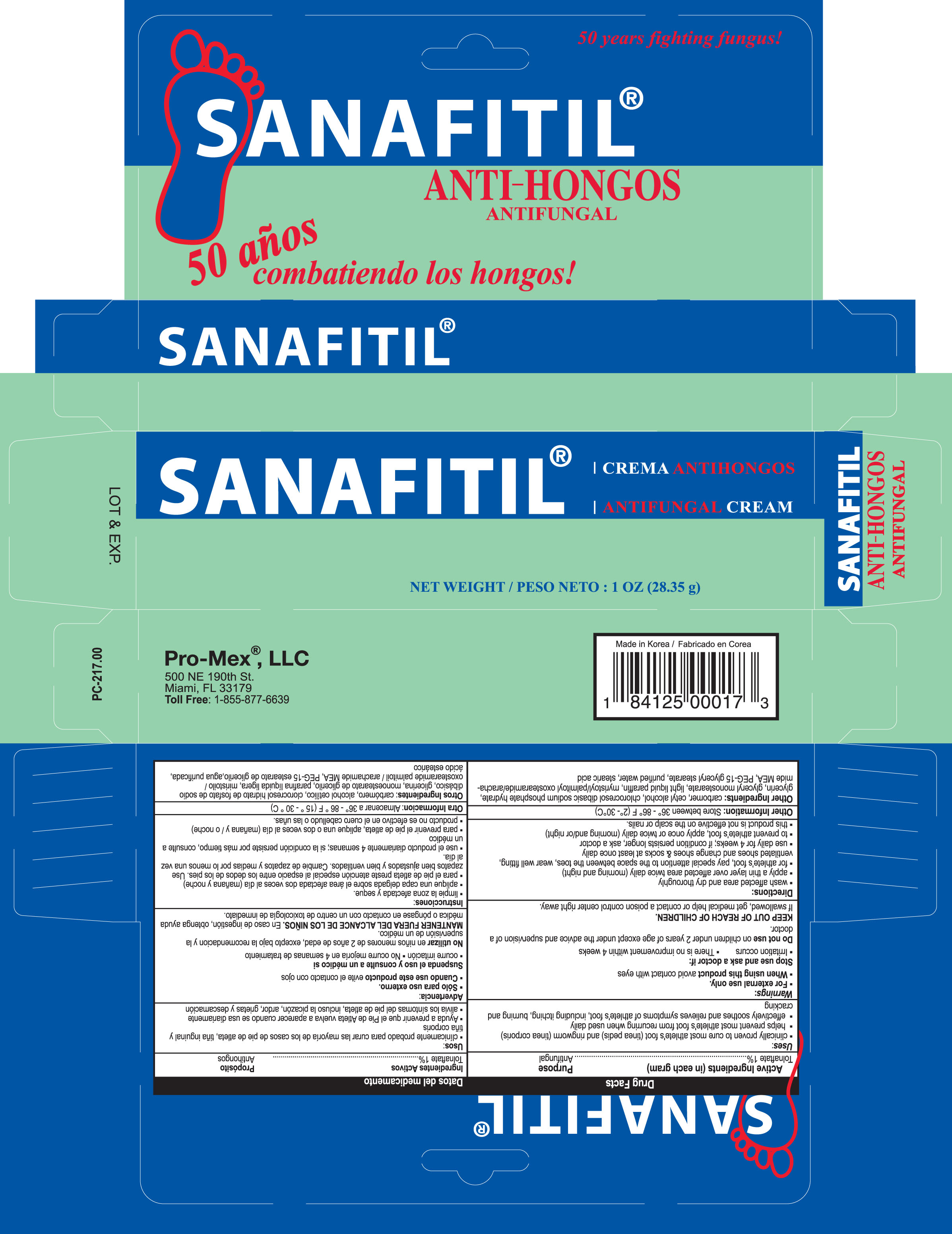 DRUG LABEL: Sanafitil Crema
NDC: 58988-1600 | Form: CREAM
Manufacturer: Promex LLC
Category: otc | Type: HUMAN OTC DRUG LABEL
Date: 20150109

ACTIVE INGREDIENTS: TOLNAFTATE 1 g/100 g
INACTIVE INGREDIENTS: CETYL ALCOHOL; GLYCERIN; GLYCERYL MONOSTEARATE; PARAFFIN; STEARIC ACID; WATER; CHLOROCRESOL; SODIUM PHOSPHATE, DIBASIC; MYRISTOYL/PALMITOYL OXOSTEARAMIDE/ARACHAMIDE MEA

Drug Facts

Active Ingredients

Tolnaftate 1%

Purpose

Antifungal

Uses

- clinically proven to cure most athlete's foot (tinea pedis) and ringworm (tinea corporis)
- helps prevnet most athlete's foot from recurring when used daily
- effectively soothes and relieves symptoms of athlete's foot, including itching, burning and cracking

Warnings

For external use only

When using this product

avoid contact with the eyes

Stop use and ask a doctor if

- irritation occurs
- there is no improvement within 4 weeks

Do not use

on children under 2 years of age except under the advice and supervision of a doctor

Keep out of reach of children

If swallowed, get medical help or contact a Poison Control Center right away.

Directions

- wash affected area and dry thoroughly
- apply a thin layer over affected area twice daily (morning and night)
- supervise children in the use of this product
- for athlete's foot, pay special attention to spaces between the toes, wear well-fitting ventilated shoes and change shoes and socks at least once daily
- use daily for 4 weeks; if condition persists longer, ask a doctor
- to prevent athlete's foot, apply once or twice daily (morning and/or night)
- this product is not effective on the scalp or nails

Inactive ingredients

Carbomer, Cetyl alcohol, Chlorocresol, Dibasic sodium phosphate hydrate, Glycerin, Glyceryl monostearate, Light liquid paraffin, Myristoyl/palmitoyl oxostearamide/arachamide MEA, PEG-15 glyceryl stearate, Stearic acid, Water

Other Information

- store between 36° and 86°F (2° and 30°C)